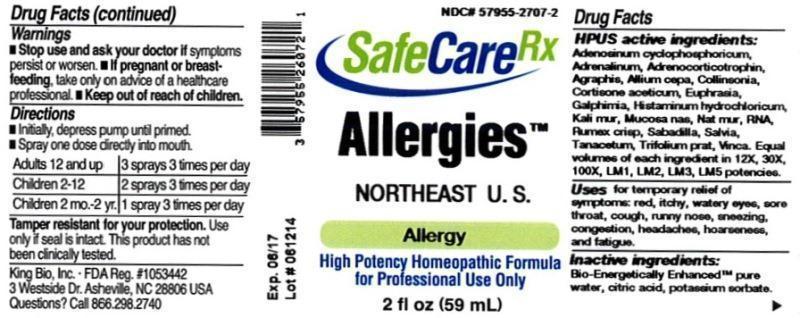 DRUG LABEL: Allergies Northeast U.S.
NDC: 57955-2707 | Form: LIQUID
Manufacturer: King Bio Inc.
Category: homeopathic | Type: HUMAN OTC DRUG LABEL
Date: 20140701

ACTIVE INGREDIENTS: ADENOSINE CYCLIC PHOSPHATE 12 [hp_X]/59 mL; EPINEPHRINE 12 [hp_X]/59 mL; CORTICOTROPIN 12 [hp_X]/59 mL; HYACINTHOIDES NON-SCRIPTA 12 [hp_X]/59 mL; ONION 12 [hp_X]/59 mL; COLLINSONIA CANADENSIS ROOT 12 [hp_X]/59 mL; CORTISONE ACETATE 12 [hp_X]/59 mL; EUPHRASIA STRICTA 12 [hp_X]/59 mL; GALPHIMIA GLAUCA FLOWERING TOP 12 [hp_X]/59 mL; HISTAMINE DIHYDROCHLORIDE 12 [hp_X]/59 mL; POTASSIUM CHLORIDE 12 [hp_X]/59 mL; SUS SCROFA NASAL MUCOSA 12 [hp_X]/59 mL; SODIUM CHLORIDE 12 [hp_X]/59 mL; SACCHAROMYCES CEREVISIAE RNA 12 [hp_X]/59 mL; RUMEX CRISPUS ROOT 12 [hp_X]/59 mL; SCHOENOCAULON OFFICINALE SEED 12 [hp_X]/59 mL; SAGE 12 [hp_X]/59 mL; TANACETUM VULGARE TOP 12 [hp_X]/59 mL; TRIFOLIUM PRATENSE FLOWER 12 [hp_X]/59 mL; VINCA MINOR 12 [hp_X]/59 mL
INACTIVE INGREDIENTS: WATER; CITRIC ACID MONOHYDRATE; POTASSIUM SORBATE

Allergies™ Northeast U.S.

ACTIVE INGREDIENT

Drug Facts__________________________________________________________________________________________________________

HPUS active ingredients: Adenosinum cyclophosphoricum, Adrenalinum, Adrenocorticotrophin, Agraphis nutans, Allium cepa, Collinsonia canadensis, Cortisone aceticum, Euphrasia officinalis, Galphimia glauca, Histaminum hydrochloricum, Kali muriaticum, Mucosa nasalis suis, Natrum muriaticum, RNA, Rumex crispus, Sabadilla, Salvia officinalis, Tanacetum vulgare, Trifolium pratense, Vinca minor. Equal volumes of each ingredient in 12X, 30X, 100X, LM1, LM2, LM3, LM5 potencies.

INDICATIONS AND USAGE

Uses for temporary relief of symptoms: red, itchy, watery eyes, sore throat, cough, runny nose, sneezing, congestion, headaches, hoarseness, and fatigue.

Inactive Ingredients:

Bio-Energetically Enhanced™ pure water, citric acid and potassium sorbate.

Warnings

- Stop use and ask your doctor if symptoms persist or worsen.
- If pregnant or breast-feeding, take only on advice of a healthcare professional.

- Keep out of reach of children.

Directions

- Initially, depress pump until primed.
- Spray one dose directly into mouth.
- Adults 12 and up: 3 sprays 3 times per day.
- Children 2-12: 2 sprays 3 times per day.
- Children 2 mo-2 yr: 1 spray 3 times per day.

OTHER SAFETY INFORMATION

Tamper resistant for your protection. Use only if seal is intact. This product has not been clinically tested.

PURPOSE

Uses for temporary relief of symptoms:

- red, itchy, watery eyes
- sore throat
- cough
- runny nose
- sneezing
- congestion
- headaches
- hoarseness
- fatigue